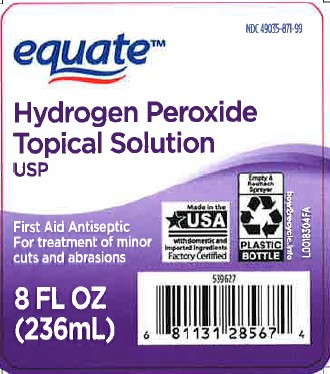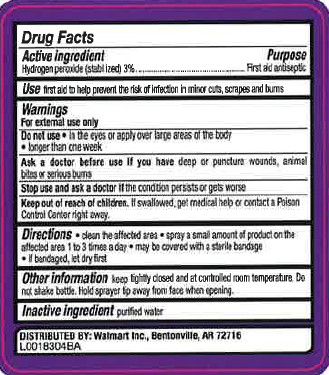 DRUG LABEL: Hydrogen Peroxide
NDC: 49035-871 | Form: SOLUTION
Manufacturer: Walmart Inc.
Category: otc | Type: HUMAN OTC DRUG LABEL
Date: 20260227

ACTIVE INGREDIENTS: HYDROGEN PEROXIDE 30 mg/1 mL
INACTIVE INGREDIENTS: WATER

Equate 871.001/871AA
3% Hydrogen Peroxide

Active ingredient

Hydrogen peroxide (stablized) 3%

Purpose

First Aid Antiseptic

Use

first aid to help prevent the risk of infection in minor cuts, scrapes and burns

Warnings

For external use only

Do not use

- in the eyes or apply over large areas of the the body
- longer than one week

Ask a doctor before use if you have

deep or puncture wounds, animal bites or serious burns

Stop use and ask a doctor if

- the condition persists or gets worse

Keep out of reach of children.

If swallowed, get medical help or contact a Poison Control Center right away.

Directions

- clean the affected area
- spray a small amount of product on the affected area 1 to 3 times a day
- may be covered with a sterile bandage
- if bandaged, let dry first

Other information

keep tightly closed and at controlled room temperature. Do not shake bottle. Hold sprayer tip away from face when opening.

Inactive ingredient

purified water

ADVERSE REACTION

DISTRIBUTED BY: Walmart Inc., Bentonville, AR 72716

principal display panel

NDC 49035-871-99

equate™

Hydrogen Peroxide

Topical Solution USP

First aid antiseptic

For treatment of minor cuts and abrasions

Made in the USA with domestic and imported ingredients

Factory Certified

Empty & Reattach Sprayer

PLASTIC BOTTLE

how2recycle.info

8 FL OZ (236 mL)